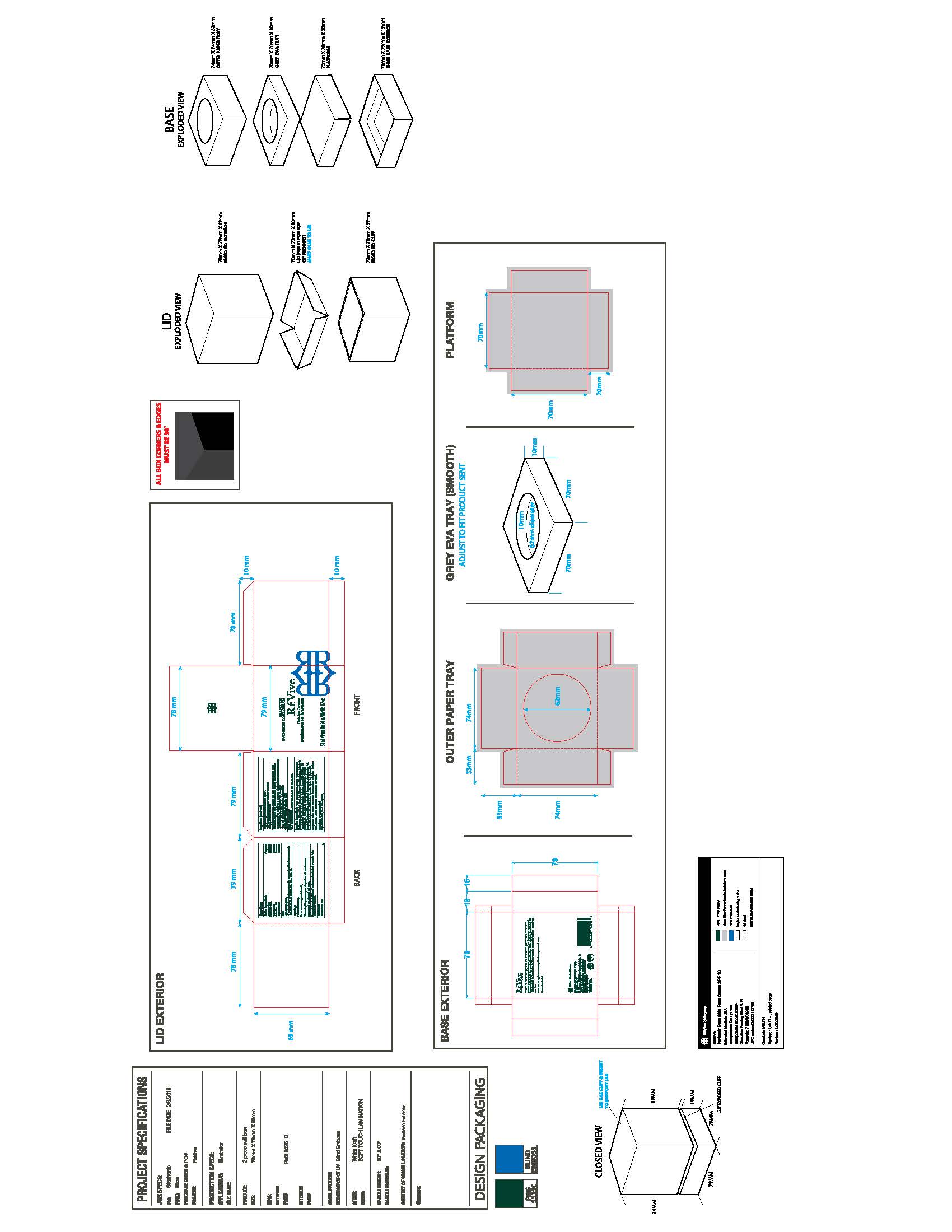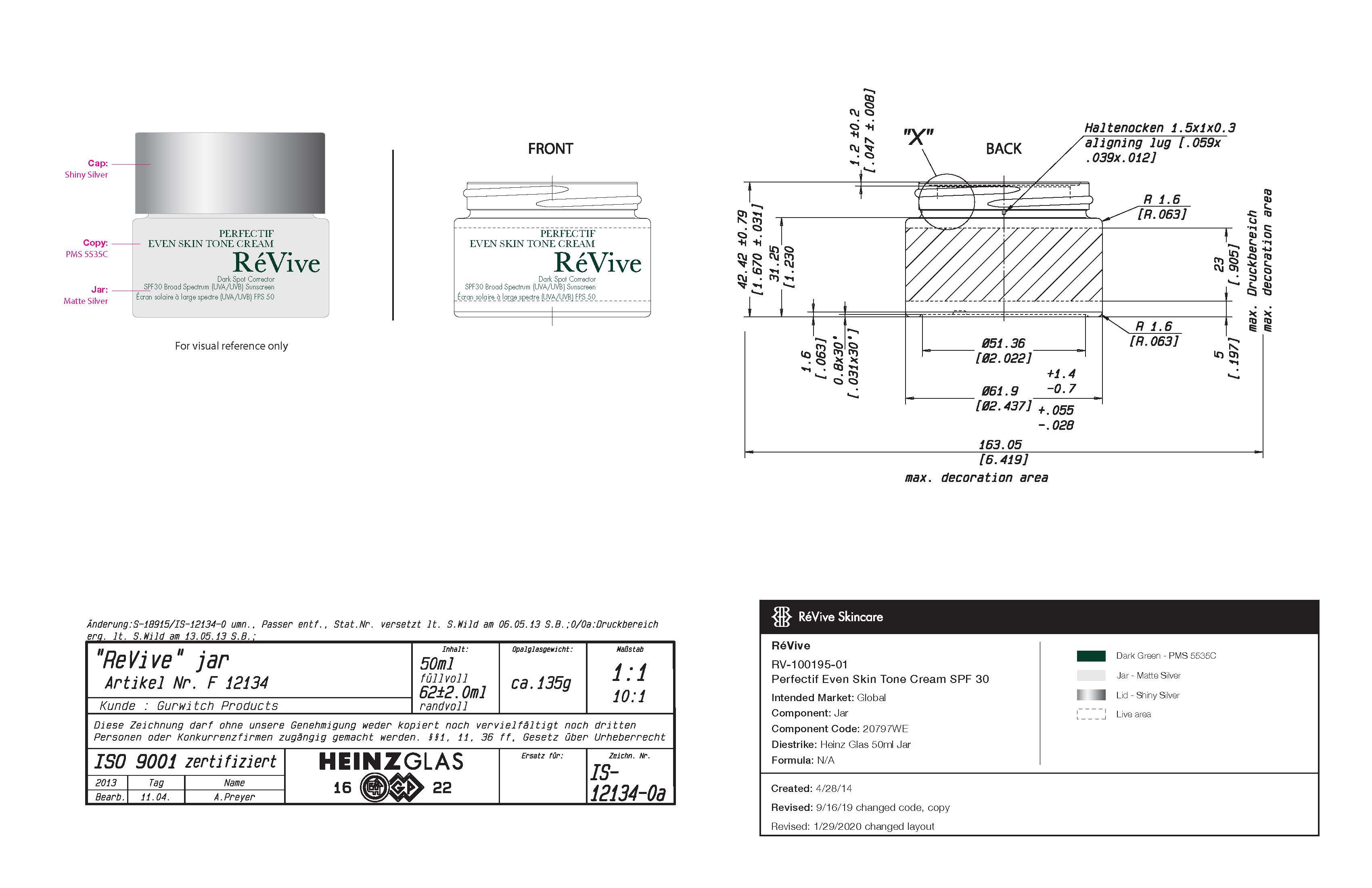 DRUG LABEL: MOISTURIZER
NDC: 61354-031 | Form: CREAM
Manufacturer: OXYGEN DEVELOPMENT, LLC
Category: otc | Type: HUMAN OTC DRUG LABEL
Date: 20230210

ACTIVE INGREDIENTS: OCTISALATE 5 mg/100 mg; AVOBENZONE 3 mg/100 mg; OXYBENZONE 5 mg/100 mg; OCTOCRYLENE 1 mg/100 mg; HOMOSALATE 10 mg/100 mg
INACTIVE INGREDIENTS: DIMETHICONE; POLYESTER-8 (1400 MW, CYANODIPHENYLPROPENOYL CAPPED); PHENOXYETHANOL; STEARIC ACID; BUTYLENE GLYCOL; SQUALANE; PHENYLETHYL RESORCINOL; GLYCERIN; WATER; POTASSIUM CETYL PHOSPHATE; PROPANEDIOL; CETOSTEARYL ALCOHOL; POLYSORBATE 60; SUNFLOWER OIL; GLYCERYL MONOSTEARATE; BETASIZOFIRAN

PERFECTIF EVEN SKIN TONE CREAM REVIVE DARK SPOT CORRECTOR SPF 30

Active Ingredients

Avobenzone 3.00%, Homosalate 10.00%, Octisalate 5.00%, Octocrylene 1.00%,Oxybenzone 5.00%.

Purpose

Sunscreen

Uses

- Helps prevent sunburn.
- If used as directed with other sun protection measures (see Directions), decreases the risk of skin cancer and early skin aging caused by the sun.

Warnings

For external use only.

Do Not Use on damaged or broken skin.

When using this product keep out of eyes. Rinse with water to remove.

Stop use

Stop use and ask a doctor if rash occurs.

Keep out of reach of children. If swallowed, get medical help or contact a Posion Contorl Center right away.

Directions

- For suncreen use:
- Apply liberally 15 minutes before sun exposure
- Use a water resistant sunscreen if swimming or sweating.
- Reapply at least every 2 hours.
- Sun Protection Measures. Spending time in the sun increases your risk of skin cancer and early skin aging. To decrease this risk, regularly use a sunscreen with a Broad Spectrum SPF value of 15 or higher and other sun protection measures including:
- Limit time in the sun, especially from 10 a.m. - 2p.m.
- Wear long-sleeved shirts, pants, hats and sunglasses
- Children under 6 months of age: Ask a doctor.

Other Information

Protect the product in this container from excessive heat and direct sun.

Inactive Ingredients

Water, Glyceryl Stearate, Glycerin, Propanediol, C12-15
Alkyl Benzoate, Cetearyl Alcohol, Stearic Acid, Butylene Glycol, Dimethicone, Polyester-8,
Polysorbate 60, Potassium Cetyl Phosphate, Helianthus Annuus (Sunflower) Seed Oil,
Oligopeptide-68, Oligopeptide-24, Phenoxyethanol, Sclerotium Gum, Phenylethyl
Resorcinol, Dimethiconol, Mica, Caprylyl Glycol, Chlorphenesin, Allantoin, Sodium PCA,
Tocopheryl Acetate, Disodium EDTA, Sodium Hydroxide, Glycine Soja (Soybean) Oil,
Hydrogenated Lecithin, Sodium Oleate, Citrus Aurantium Dulcis (Orange) Oil, Tocopherol,
Citral, Limonene, Linalool. May Contain: Titanium Dioxide, Iron Oxides.

Primary package

50ml, 61354-031-01

Secondary package

50ml, 61354-031-01